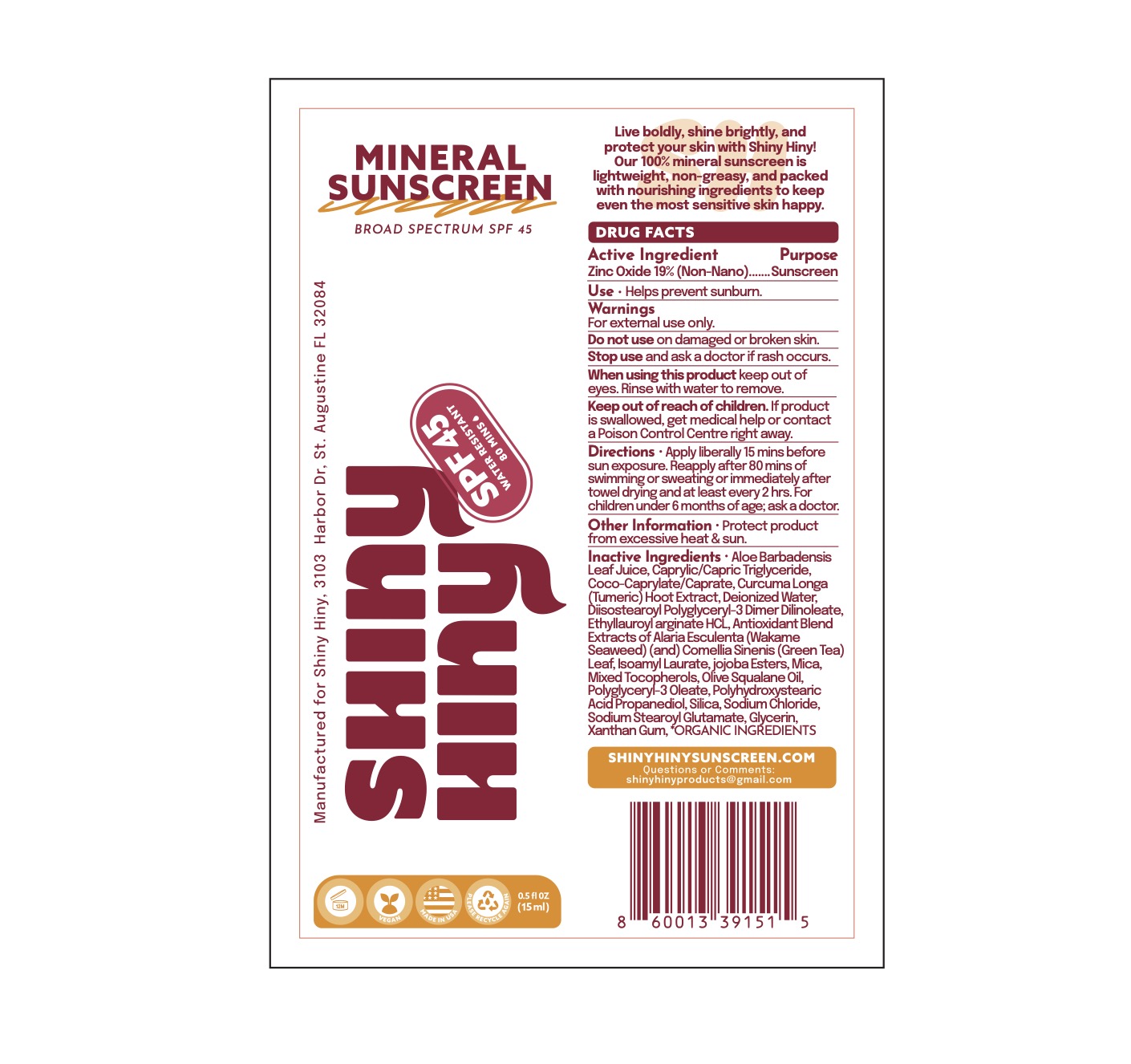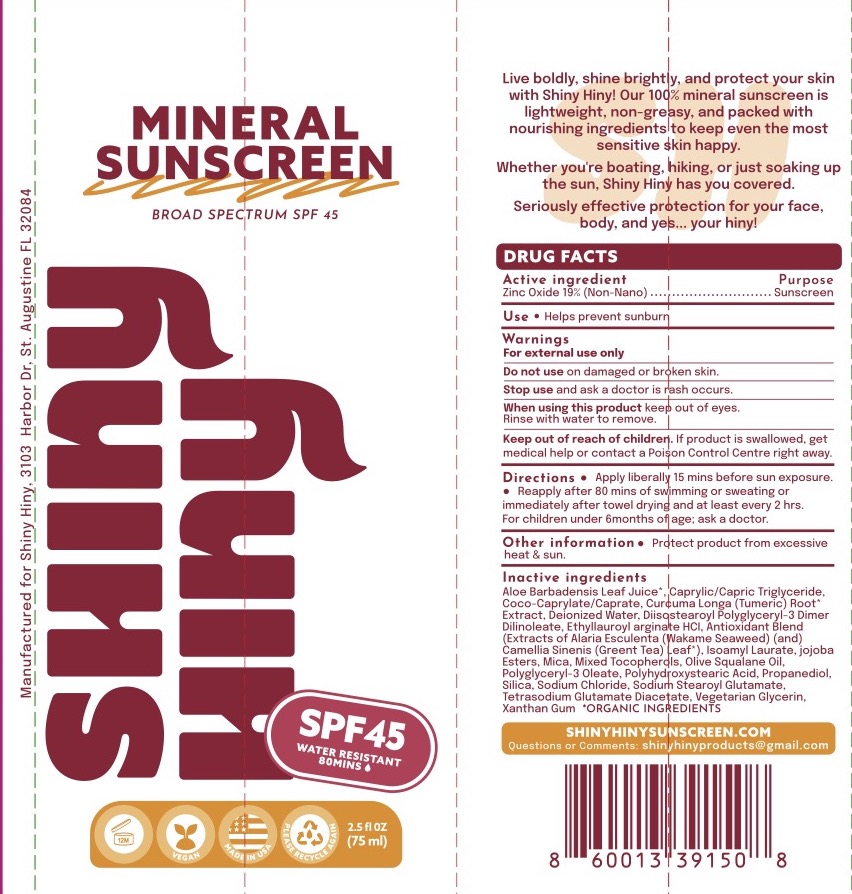 DRUG LABEL: Shiny Hiny SPF 45 Mineral Sunscreen
NDC: 85465-045 | Form: LOTION
Manufacturer: Shiny Hiny Products, LLC
Category: otc | Type: HUMAN OTC DRUG LABEL
Date: 20260203

ACTIVE INGREDIENTS: ZINC OXIDE 19 g/100 mL
INACTIVE INGREDIENTS: ETHYL LAUROYL ARGINATE HYDROCHLORIDE; POLYHYDROXYSTEARIC ACID (2300 MW); PROPANEDIOL; DIISOSTEAROYL POLYGLYCERYL-3 DIMER DILINOLEATE; OLEA EUROPAEA LEAF; TOCOPHEROL; GREEN TEA LEAF; ISOAMYL LAURATE; MEDIUM-CHAIN TRIGLYCERIDES; ALARIA ESCULENTA; SQUALANE; POLYGLYCERYL-3 OLEATE; MICA; SODIUM CHLORIDE; GLYCERIN; XANTHAN GUM; COCONUT OIL; JOJOBA OIL, RANDOMIZED; HOLY BASIL LEAF; WATER; COCO-CAPRYLATE/CAPRATE; TETRASODIUM GLUTAMATE DIACETATE; ALOE VERA LEAF; TURMERIC; SODIUM STEAROYL GLUTAMATE; SILICON DIOXIDE

Shiny Hiny SPF 45 Mineral Sunscreen

ACTIVE INGREDIENT

Zinc Oxide 19%

PURPOSE

Sunscreen.

INDICATIONS AND USAGE

Helps prevent sunburn.

WARNINGS

For external use only.

Do no use on damaged or broken skin.

Stop use and ask a doctor if rash occurs.

When using this product keep out of eyes. Rinse with water to remove.

KEEP OUT OF REACH OF CHILDREN

If product is swallowed, get medical help or contact a Poison Control Center right away.

DOSAGE AND ADMINISTRATION

Apply liberally 15 minutes before sun exposure. Reapply after 80 minutes of swimming or sweating or immediately after towel drying and at lease every 2 hours.

For children under 6 months of age: ask a doctor.

INACTIVE INGREDIENT

Aloe Barbadensis (Aloe) Leaf Juice*, Caprylic/Capric Triglyceride, Coco-Caprylate/Caprate, Curcuma Longa (Turmeric) Root Extract*, Deionized Water, Diisostearoyl Polyglycery-3 Dimer Dilinoleate, Ethyl Lauroyl Arginate HCl, Extracts of Alaria Esculenta (Wakame Seaweed), Camelia Sinensis (Green Tea) Leaf*, Ocimum Tenuiflorum (Tulsi) Leaf*, Olea Europa (Olive) Leaf* in Cocos Nucifera (Coconut) Oil, Iron Oxides (CI 77492, CI 77491, CI 77499), Isoamyl Laurate, Jojoba Esters, Mica, Mixed Tocopherols, Olive Squalane Oil, Polyglyceryl-3 Oleate, Polyhydroxystearic Acid, Olive Squalane Oil, Polyglceryl-3 Oleate, Polyhydroxystearic Acid, Propanediol, Silica, Sodium Chloride, Sodium Stearoyl Glutamate, Tetrasodium Glutamate Diacetate, Vegetarian Glycerin, Xanthan Gum, *ORGANIC INGREDIENTS